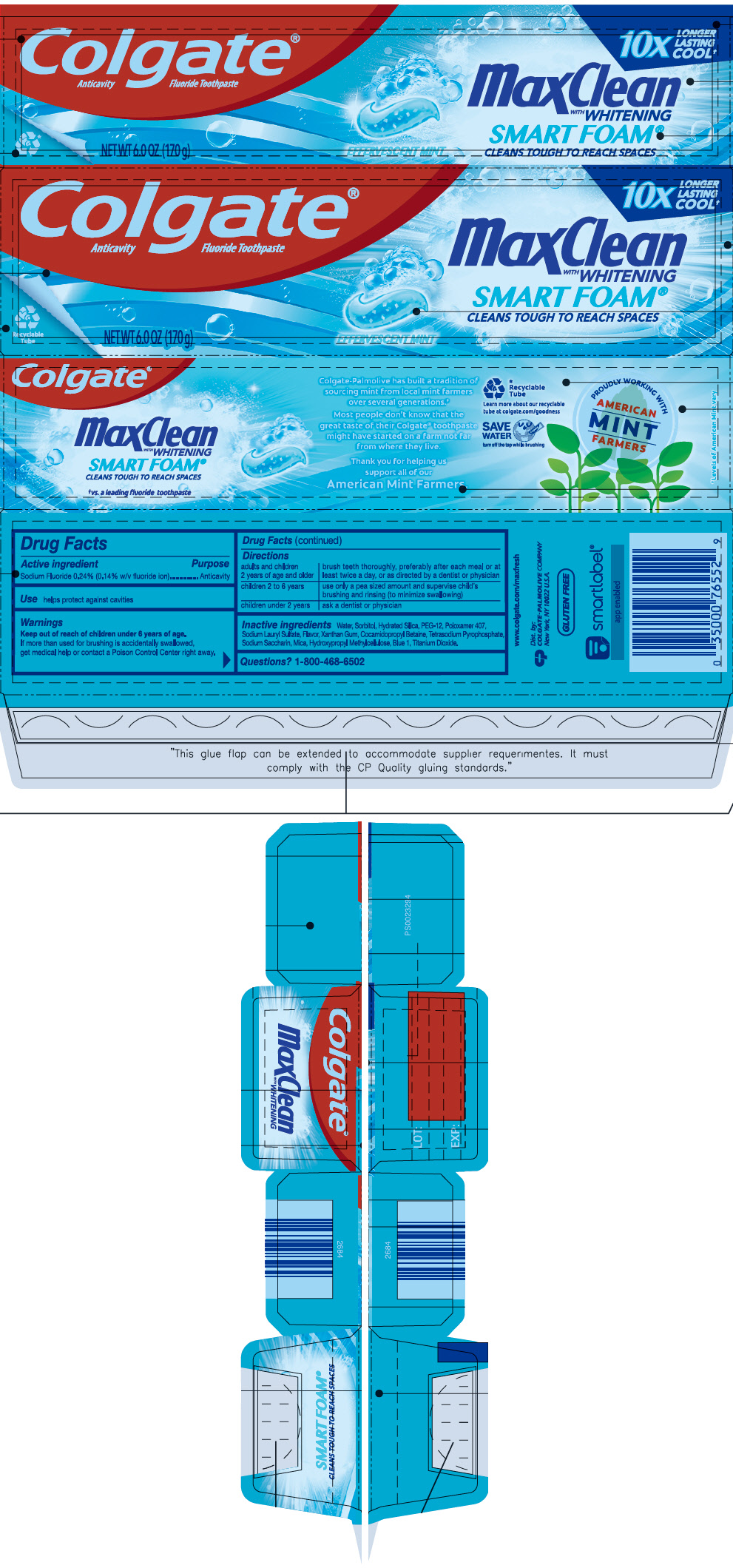 DRUG LABEL: Colgate
NDC: 35000-930 | Form: GEL, DENTIFRICE
Manufacturer: Colgate-Palmolive Company
Category: otc | Type: HUMAN OTC DRUG LABEL
Date: 20241113

ACTIVE INGREDIENTS: SODIUM FLUORIDE 1.1 mg/1 g
INACTIVE INGREDIENTS: SORBITOL 347 mg/1 g; WATER; HYDRATED SILICA; POLYETHYLENE GLYCOL 600; POLOXAMER 407; SODIUM LAURYL SULFATE; XANTHAN GUM; COCAMIDOPROPYL BETAINE; SODIUM PYROPHOSPHATE; MICA; TITANIUM DIOXIDE; SACCHARIN SODIUM; METHYLCELLULOSE (400 MPA.S); FD&C BLUE NO. 1

Colgate® Max Clean™ Effervescent mint™ Fluoride Toothpaste

Drug Facts

Active ingredient

Sodium fluoride 0.24% (0.14% w/v fluoride ion)

Purpose

Anticavity

Use

helps protect against cavities

Warnings

Keep out of reach of children under 6 years of age.

If more than used for brushing is accidentally swallowed, get medical help or contact a Poison Control Center right away.

Directions

adults and children 2 years of age and older | brush teeth thoroughly, preferably after each meal or at least twice a day, or as directed by a dentist or physician
children 2 to 6 years | use only a pea sized amount and supervise child's brushing and rinsing (to minimize swallowing)
children under 2 years | ask a dentist or physician

Inactive ingredients

water, sorbitol, hydrated silica, PEG-12, poloxamer 407, sodium lauryl sulfate, flavor, xanthan gum, cocamidopropyl betaine, tetrasodium pyrophosphate, sodium saccharin, methylcellulose, mica, titanium dioxide, FD&C blue no. 1

Questions?

1-800-468-6502

Dist. by:
COLGATE-PALMOLIVE CO.
New York, NY 10022

PRINCIPAL DISPLAY PANEL - 170 g Tube Carton

Colgate®
Anticavity Fluoride Toothpaste

10X
LONGER
LASTING
COOL†

MaxClean
WITH WHITENING
SMART FOAM®
CLEANS TOUGH TO REACH SPACES

Recyclable
Tube

NET WT 6.0 OZ (170 g)

EFFERVESCENT MINT